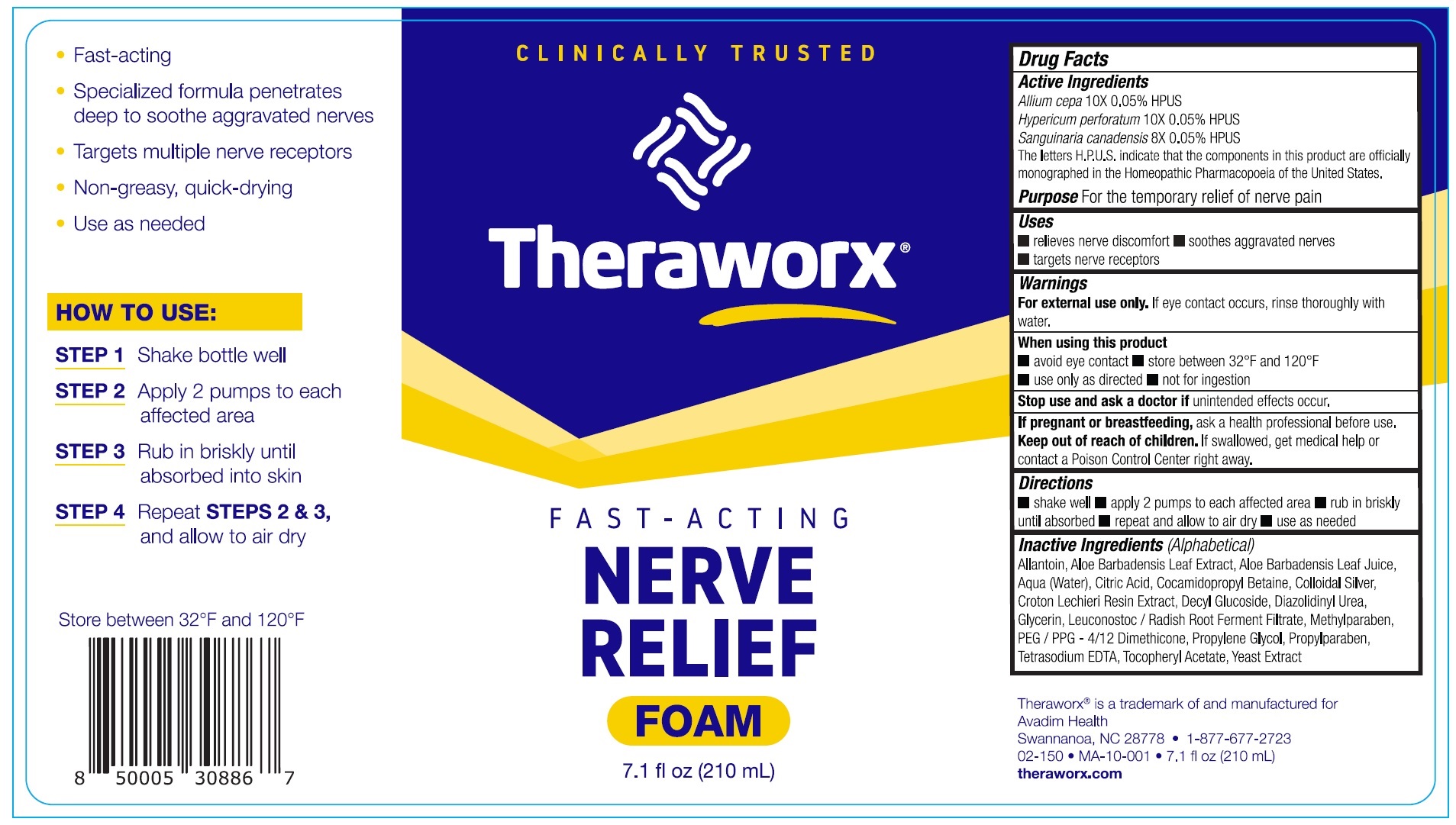 DRUG LABEL: Theraworx Nerve Relief Foam
NDC: 61594-020 | Form: AEROSOL, FOAM
Manufacturer: AVADIM HOLDINGS, INC.
Category: homeopathic | Type: HUMAN OTC DRUG LABEL
Date: 20230425

ACTIVE INGREDIENTS: ONION 10 [hp_X]/1 mL; HYPERICUM PERFORATUM WHOLE 10 [hp_X]/1 mL; SANGUINARIA CANADENSIS ROOT 8 [hp_X]/1 mL
INACTIVE INGREDIENTS: ALOE VERA LEAF; ALLANTOIN; WATER; CITRIC ACID MONOHYDRATE; COCAMIDOPROPYL BETAINE; SILVER; CROTON LECHLERI RESIN; DECYL GLUCOSIDE; DIAZOLIDINYL UREA; GLYCERIN; LEUCONOSTOC/RADISH ROOT FERMENT FILTRATE; METHYLPARABEN; PEG/PPG-4/12 DIMETHICONE; PROPYLENE GLYCOL; PROPYLPARABEN; EDETATE SODIUM; .ALPHA.-TOCOPHEROL ACETATE; YEAST, UNSPECIFIED

Theraworx Nerve Relief Foam

Active Ingredients

Allium cepa 10X 0.05% HPUS

Hypericum perforatum 10X 0.05% HPUS

Sanguinaria canadensis 8X 0.05% HPUS

The letters H.P.U.S. indicate that the components in this product are officially monographed in the Homeopathic Pharmacopoeia of the United States.

Purpose

For the temporary relief of nerve pain

Uses

- relieves nerve discomfort
- soothes aggravated nerves
- targets nerve receptors

Warnings

For external use only. If eye contact occurs, rinse thoroughly with water.

When using this product

- avoid eye contact
- store between 32ºF and 120ºF
- ues only as directed
- not for ingestion

Stop use and ask a doctor if

unintended effects occurs.

If pregnant or breastfeeding,

ask a health professional before use.

Keep out of reach of chidlren.

If swallowed, get medical help or contact a Poison Control right away.

Directions

- shake well
- apply 2 pumps to each affected area
- rub in briskly until absorbed
- repeat and allow to air dry
- use as needed

Inactive Ingredients (Alphabetical)

Allantoin, Aloe Barbadensis Leaf Extract, Aloe Barbadensis Leaf Juice, Aqua (Water), Citric Acid, Cocamidopropyl Betaine, Colloidal Silver, Croton Lechieri Resin Extract, Decyl Glucoside, Diazolidinyl Urea, Glycerin, Leuconostoc/ Radish Root Ferment Filtrate, Methylparaben, PEG / PPG - 4/12 Dimethicone, Propylene Glycol, Propylparaben, Tetrasodium EDTA, Tocopheryl Acetate, Yeast Extract